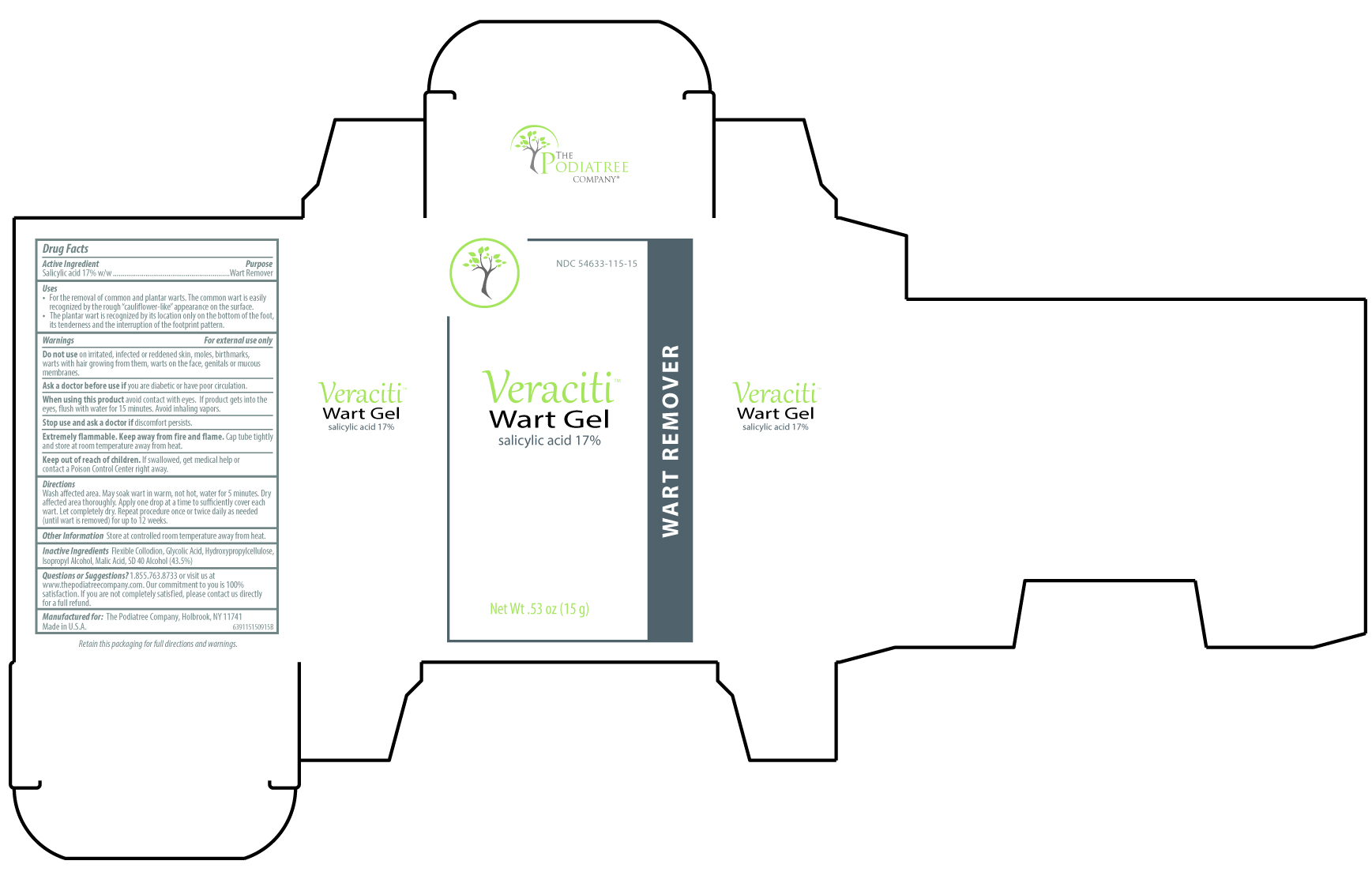 DRUG LABEL: Veraciti
NDC: 54633-115 | Form: GEL
Manufacturer: The Podiatree Company
Category: otc | Type: HUMAN OTC DRUG LABEL
Date: 20260108

ACTIVE INGREDIENTS: SALICYLIC ACID 17 g/100 g
INACTIVE INGREDIENTS: ALCOHOL; ISOPROPYL ALCOHOL; PYROXYLIN; GLYCOLIC ACID; HYDROXYPROPYL CELLULOSE (1600000 WAMW); MALIC ACID

Veraciti

Active ingredient

Salicylic acid 17% w/w

Purpose

Wart Remover

Uses

- For the removal of common and plantar warts. The common wart is easily recognized by the rough “cauliflower-like” appearance on the surface.
- The plantar wart is recognized by its location only on the bottom of the foot, its tenderness and the interruption of the footprint pattern.

Warnings

For external use only.

Do not use

on irritated, infected or reddened skin, moles, birthmarks, warts with hair growing from them, warts on the face, genitals or mucous membranes.

Ask a doctor before use if

you are diabetic or have poor circulation.

When using this product

avoid contact with eyes. If product gets into the eye, flush with water for 15 minutes. Avoid inhaling vapors.

Stop use and ask a doctor if

discomfort persists.

Extremely flammable.

Keep away from fire and flame. Cap tube tightly and store at room temperature away from heat.

Keep out of reach of children.

If swallowed, get medical help or contact a Poison Control Center right away.

Directions

Wash affected area. May soak wart in warm, not hot, water for 5 minutes. Dry affected area thoroughly. Apply one drop at a time to suffciently cover each wart. Let completely dry. Repeat procedure once or twice daily as needed (until wart is removed) for up to 12 weeks.

Inactive ingredients

Flexible Collodion, Glycolic Acid, Hydroxypropylcellulose, Isopropyl Alcohol, Malic Acid, SD 40 Alcohol (43.5%)

Questions or Suggestions?

1.855.763.8733 or visit us at www.thepodiatreecompany.com. Our commitment to you is 100% satisfaction. If you are not

completely satisfied, please contact us directly for a full refund.